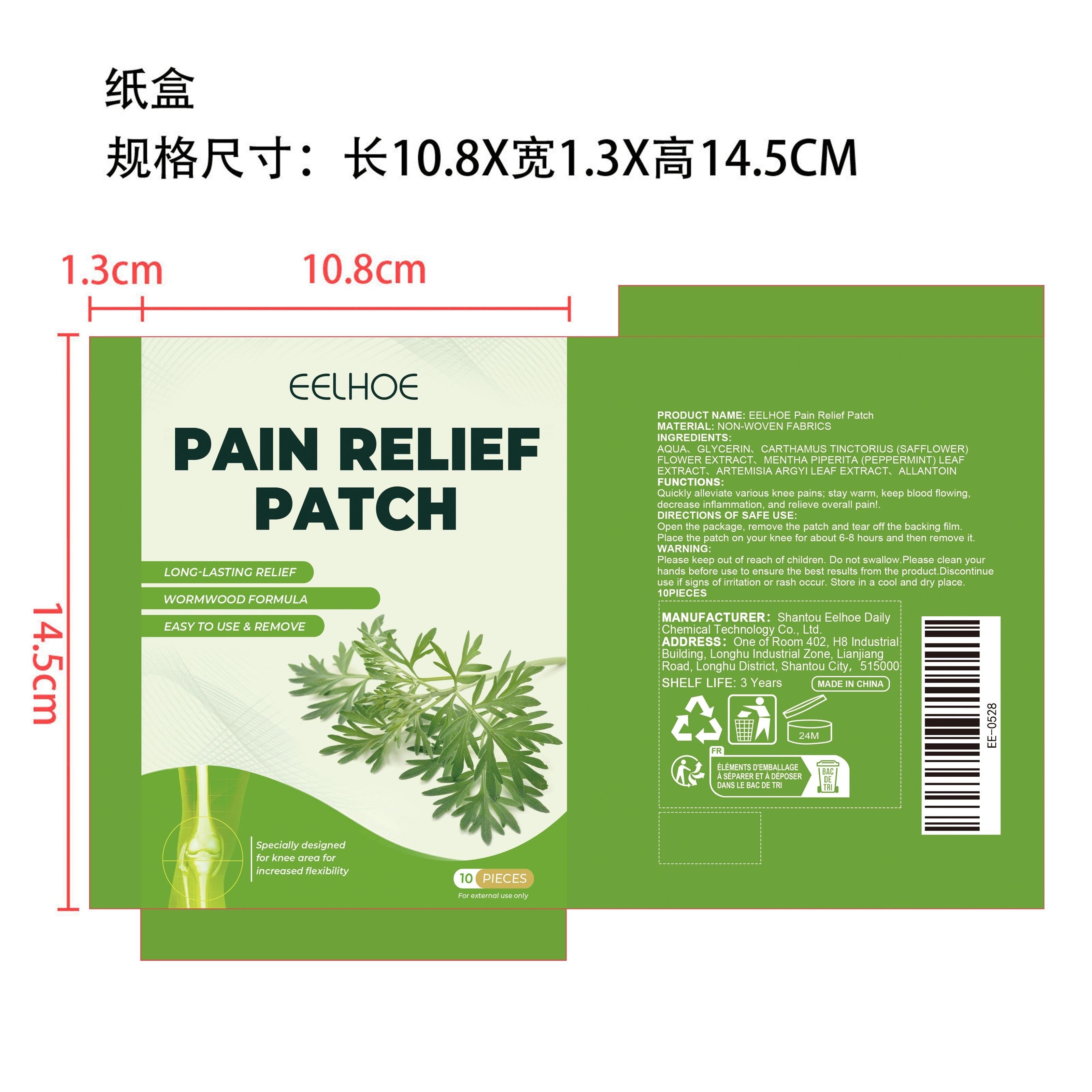 DRUG LABEL: EELHOE Pain Relief Patch
NDC: 85064-013 | Form: PATCH
Manufacturer: Shantou Eelhoe Daily Chemical Technology Co., Ltd.
Category: otc | Type: HUMAN OTC DRUG LABEL
Date: 20251127

ACTIVE INGREDIENTS: ARTEMISIA ARGYI LEAF 0.002 mg/10 mg; MENTHA PIPERITA (PEPPERMINT) LEAF 0.002 mg/10 mg; CARTHAMUS TINCTORIUS (SAFFLOWER) FLOWER 0.005 mg/10 mg
INACTIVE INGREDIENTS: GLYCERIN 0.5 mg/10 mg; ALLANTOIN 0.002 mg/10 mg; AQUA 9.489 mg/10 mg

ACTIVE INGREDIENT

CARTHAMUS TINCTORIUS (SAFFLOWER) FLOWER EXTRACT、MENTHA PIPERITA (PEPPERMINT) LEAF EXTRACT、ARTEMISIA ARGYI LEAF EXTRACT

WHEN USING

Open the package, remove the patch and tear off the backing film. Place the patch on any desired location on your body and remove it after about 6-8 hours.

PURPOSE

1. The patch can penetrate deeply and help you regain health and live a relaxed and happy life.

2. Using mugwort extract can relax your joints or muscles and give your body a full rest.

3. Using plant extracts, the ingredients are mild and safe, have no side effects, and are suitable for use by all kinds of people.

WARNINGS

Please keep out of reach of children. Do not swallow.Please clean your hands before use to ensure the best results from the product. Discontinue use if signs of irritation or rash occur. Store in a cool and dry place.

DO NOT USE

Discontinue use if signs of irritation or rash occur.

STOP USE

Discontinue use if signs of irritation or rash occur.

KEEP OUT OF REACH OF CHILDREN

Please keep out of reach of children. Do not swallow.

STORAGE AND HANDLING

Store in a cool and dry place.

INACTIVE INGREDIENT

AQUA、GLYCERIN、ALLANTOIN

DOSAGE AND ADMINISTRATION

Open the package, remove the patch and tear off the backing film. Place the patch on any desired location on your body and remove it after about 6-8 hours.

INDICATIONS AND USAGE

Open the package, remove the patch and tear off the backing film. Place the patch on any desired location on your body and remove it after about 6-8 hours.